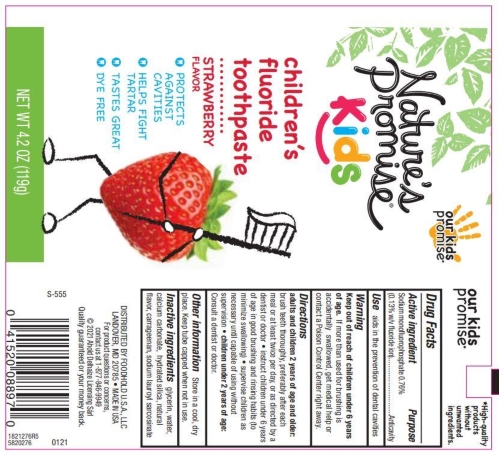 DRUG LABEL: Natures Promise
NDC: 41520-724 | Form: PASTE, DENTIFRICE
Manufacturer: Foodhold U.S.A.
Category: otc | Type: HUMAN OTC DRUG LABEL
Date: 20250808

ACTIVE INGREDIENTS: SODIUM MONOFLUOROPHOSPHATE 0.13 g/100 g
INACTIVE INGREDIENTS: GLYCERIN; CARRAGEENAN; CALCIUM CARBONATE; HYDRATED SILICA; WATER; SODIUM LAUROYL SARCOSINATE

5820276 Nature's Promise Kids Fluoride TP Strawberry

Active ingredient

Sodium Monofluorophosphate 0.76% w/w (0.13% w/v fluoride ion)

Drug Facts

Purpose

Anticavity

Use

helps protect against cavities

Warnings

Keep out of reach of children under 6 years of age. If more than used for brushing is accidentally swallowed, get medical help or contact a Poison Control Center right away.

Directions

Adults and children 2 years of age and older: brush teeth thorughly preferably after each meal or at least twice a day, or as directed by a dentist or doctor.

Children 2 to 6 years: use a pea-sized amount and supervise child's brushing and rinsing (to minimize swallowing).

Children under 2 years of age: consult a dentist or physician.

INACTIVE INGREDIENT

Inactive ingredients glycerin, water, calcium carbonate, hydrated silica, natural flavor, carrageenan, sodium lauroyl sarcosinate

Other information

Store in a cool dry place. Keep tube capped when not in use.

DISTRIBUTED BY: FOODHOLD U.S.A., LLC

LANDOVER, MD 20785 • 1-877-846-6649

PACKAGE LABEL

Nature's Promise

children's fluoride toothpaste

strawberry

- protects against cavities
- tastes great
- helps fight tartar

NET WT 4.2 OZ (119 g)